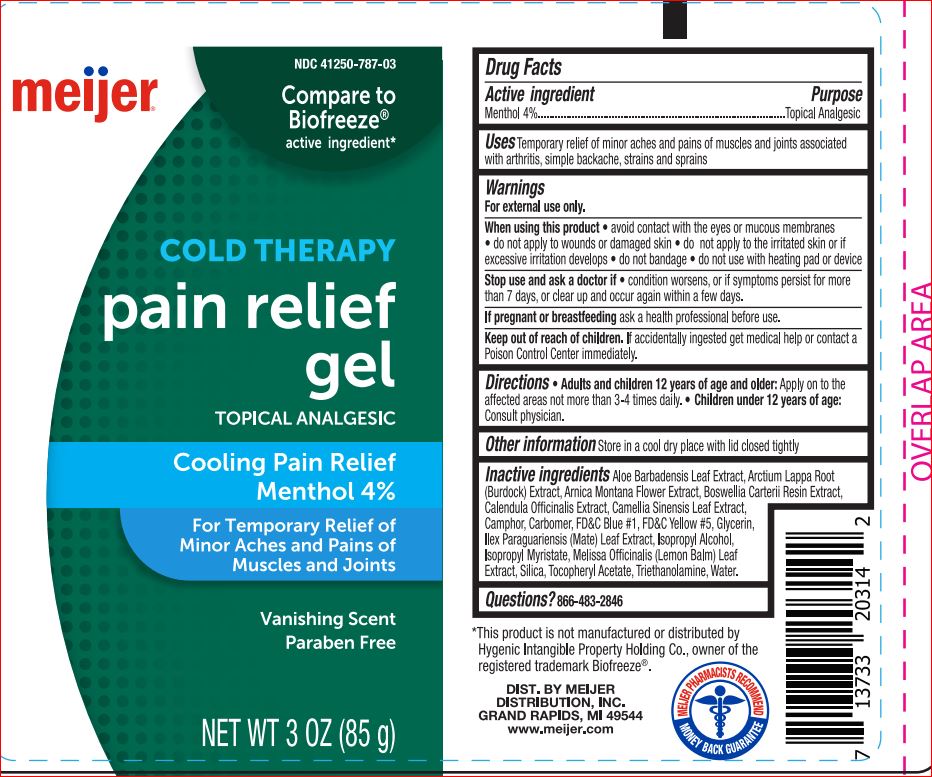 DRUG LABEL: Cold Therapy Pain Relief
NDC: 41250-787 | Form: GEL
Manufacturer: Meijer
Category: otc | Type: HUMAN OTC DRUG LABEL
Date: 20180712

ACTIVE INGREDIENTS: Menthol 4 g/100 g
INACTIVE INGREDIENTS: ALOE VERA LEAF; ARCTIUM LAPPA ROOT; ARNICA MONTANA FLOWER; FRANKINCENSE; CALENDULA OFFICINALIS FLOWER; GREEN TEA LEAF; CAMPHOR (SYNTHETIC); CARBOMER HOMOPOLYMER TYPE C (ALLYL PENTAERYTHRITOL CROSSLINKED); FD&C BLUE NO. 1; FD&C YELLOW NO. 5; Glycerin; ILEX PARAGUARIENSIS LEAF; Isopropyl Alcohol; Isopropyl Myristate; MELISSA OFFICINALIS LEAF; SILICON DIOXIDE; .ALPHA.-TOCOPHEROL ACETATE; TROLAMINE; Water

Drug Facts

Active ingredient Purpose
Menthol 4%..........................................................Topical Analgesic

Uses
Temporary relief of minor aches and pains of muscles and joints
associated with arthritis, simple backache, strains and sprains

Warnings
For external use only.
When using this product • avoid contact with the eyes or mucous
membranes • do not apply to wounds or damaged skin • do not
apply to the irritated skin or if excessive irritation develops • do not
bandage • do not use with heating pad or device
Stop use and ask a doctor if • condition worsens, or if symptoms
persist for more than 7 days, or clear up and occur again within a
few days.
If pregnant or breastfeeding ask a health professional before use

Keep out of reach of children. If accidentally ingested get
medical help or contact a Poison Control Center immediately.

Directions
• Adults and children 12 years of age and older: Apply on to the
affected areas not more than 3-4 times daily.
• Children under 12 years of age: Consult physician

Other information
Store in a cool dry place with lid closed tightly

Inactive ingredients
Aloe Barbadensis Leaf Extract, Arctium Lappa Root (Burdock)
Extract, Arnica Montana Flower Extract, Boswellia Carterii Resin
Extract, Calendula Officinalis Extract, Camellia Sinensis Leaf Extract,
Camphor, Carbomer, FD&C Blue #1, FD&C Yellow #5, Glycerin, Ilex
Paraguariensis (Mate) Leaf Extract, Isopropyl Alcohol, Isopropyl
Myristate, Melissa Officinalis (Lemon Balm) Leaf Extract, Silica,
Tocopheryl Acetate, Triethanolamine, Water.

Questions? 866-483-2846